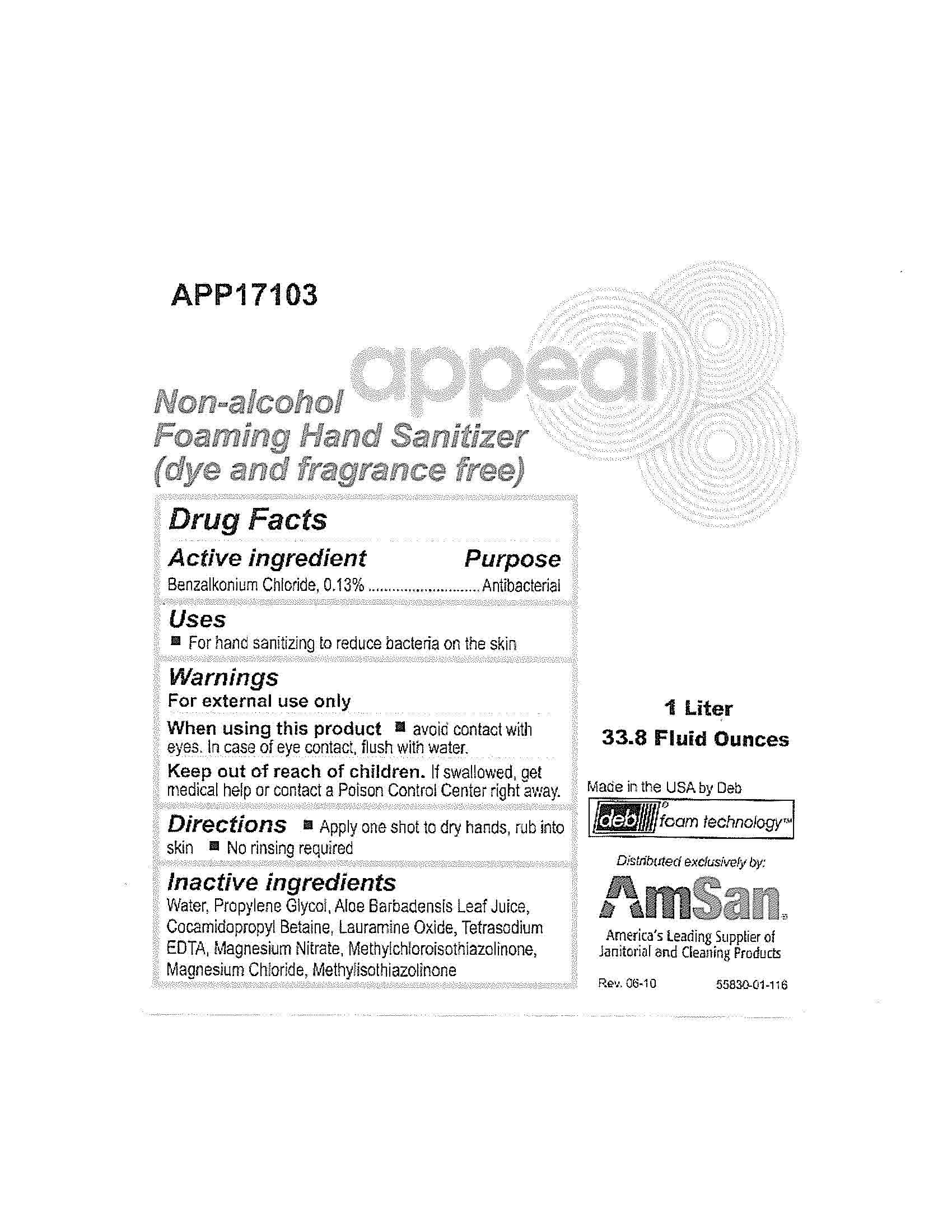 DRUG LABEL: Appeal Non-Alcohol Foaming Hand Sanitizer
NDC: 11084-106 | Form: LIQUID
Manufacturer: Deb USA, Inc.
Category: otc | Type: HUMAN OTC DRUG LABEL
Date: 20100930

ACTIVE INGREDIENTS: BENZALKONIUM CHLORIDE 0.13 mL/100 mL
INACTIVE INGREDIENTS: WATER; PROPYLENE GLYCOL; ALOE VERA LEAF; COCAMIDOPROPYL BETAINE; LAURAMINE OXIDE; EDETATE SODIUM; MAGNESIUM NITRATE; METHYLCHLOROISOTHIAZOLINONE; MAGNESIUM CHLORIDE; METHYLISOTHIAZOLINONE

Drug Facts

Acitive ingredient

Benzalkonium Chloride, 0.13%

Purpose

Antibacterial

Uses

For hand sanitizing to reduce bacteria on the skin

Warnings

For external use only

When using this product avoid contact with eyes.

In case of contact, flush with water.

Keep out of reach of children.

If swallowed, get medical help or contact a Poison Control Center right away.

Directions

Apply one shot to dry hands, rub into skin

No rinsing required

Inactive ingredients

Water, Propylene Glycol, Aloe Barbadensis Leaf Juice, Cocamidopropyl Betaine, Lauramine Oxide, Tetrasodium EDTA, Magnesium Nitrate, Methylchloroisothiazolinone, Magnesium Chloride, Methylisothiazolinone

PACKAGE LABEL

APP17103

appeal

Non-alcohol Foaming Hand Sanitizer

1 Liter

33.8 Fluid Ounces

Made in the USA by Deb

deb foam technology

Distributed exclusively by:

AmSan

America's Leading Supplier of Janitorial and Cleaning Products